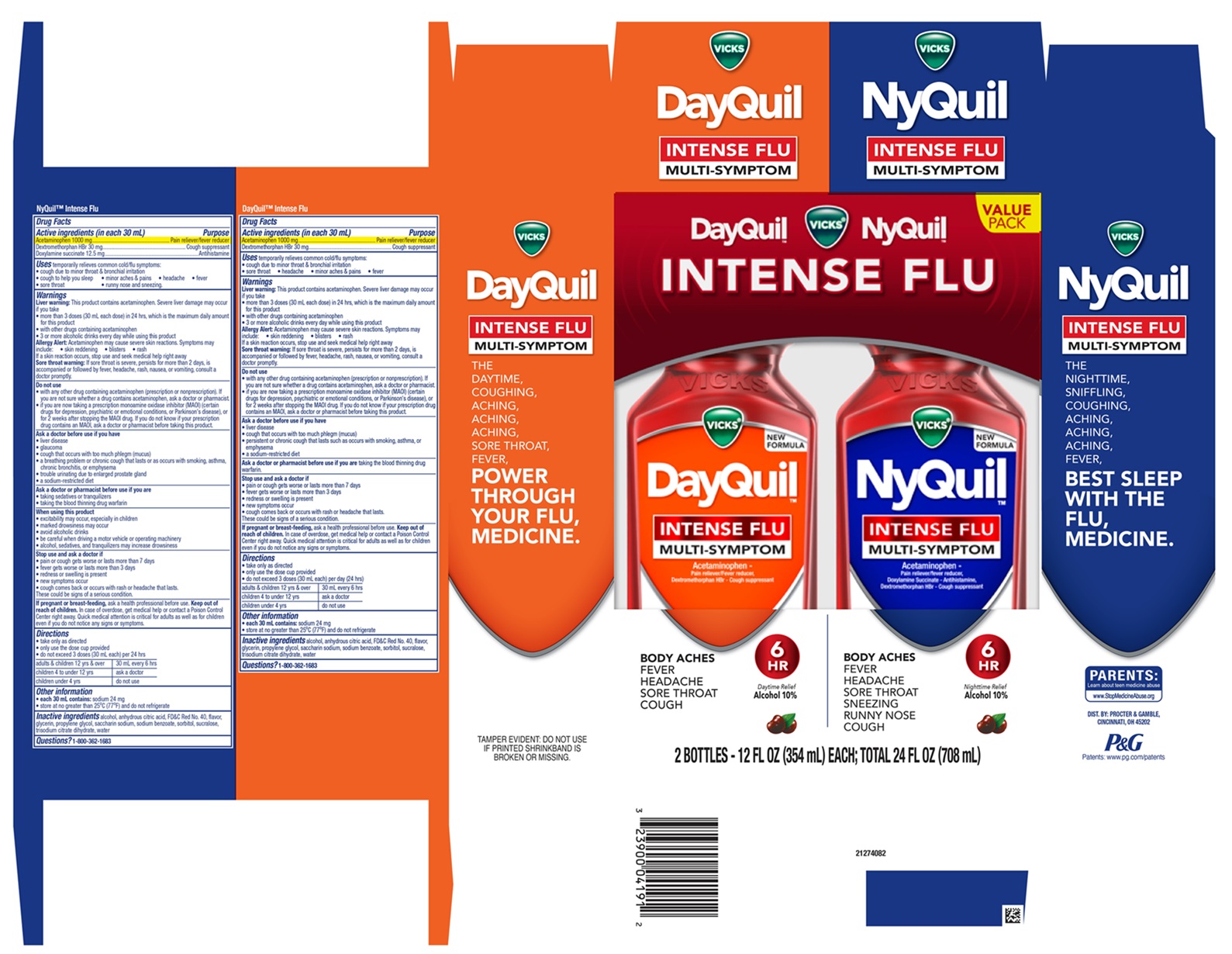 DRUG LABEL: Vicks DayQuil and Vicks NyQuil
NDC: 84126-358 | Form: KIT | Route: ORAL
Manufacturer: The Procter & Gamble Manufacturing Company
Category: otc | Type: HUMAN OTC DRUG LABEL
Date: 20250414

ACTIVE INGREDIENTS: ACETAMINOPHEN 1000 mg/30 mL; DEXTROMETHORPHAN HYDROBROMIDE 30 mg/30 mL; DEXTROMETHORPHAN HYDROBROMIDE 30 mg/30 mL; DOXYLAMINE SUCCINATE 12.5 mg/30 mL; ACETAMINOPHEN 1000 mg/30 mL
INACTIVE INGREDIENTS: GLYCERIN; ANHYDROUS CITRIC ACID; PROPYLENE GLYCOL; FD&C RED NO. 40; WATER; SACCHARIN SODIUM; SODIUM BENZOATE; SORBITOL; TRISODIUM CITRATE DIHYDRATE; SUCRALOSE; ALCOHOL; FD&C RED NO. 40; ALCOHOL; PROPYLENE GLYCOL; WATER; SACCHARIN SODIUM; SODIUM BENZOATE; SUCRALOSE; SORBITOL; GLYCERIN; TRISODIUM CITRATE DIHYDRATE; ANHYDROUS CITRIC ACID

Vicks® DayQuil™ and NyQuil™ INTENSE FLU MULTI-SYMPTOM Liquid Convenience Pack

Vicks® NyQuil™ INTENSE FLU MULTI-SYMPTOM Liquid

Drug Facts

Active ingredients (in each 30 mL)

Acetaminophen 1000 mg

Dextromethorphan HBr 30 mg

Doxylamine succinate 12.5 mg

Purpose

Pain reliever/ fever reducer
Cough suppressant
Antihistamine

Uses

temporarily relieves common cold/flu symptoms:

- cough due to minor throat & bronchial irritation
- cough to help you sleep
- sore throat
- headache
- minor aches & pains
- fever
- runny nose & sneezing

Warnings

Liver warning:

This product contains acetaminophen. Severe liver damage may occur if you take
• more than 3 doses (30 mL each) in 24 hrs, which is the maximum daily amount for this product
• with other drugs containing acetaminophen
• 3 or more alcoholic drinks every day while using this product

Allergy Alert: Acetaminophen may cause severe skin reactions. Symptoms may include:
• skin reddening • blisters • rash

If a skin reaction occurs, stop use and seek medical help right away

Sore throat warning: If sore throat is severe, persists for more than 2 days, is accompanied or followed by fever, headache, rash, nausea, or vomiting, consult a doctor promptly.

If sore throat is severe, persists for more than 2 days, is accompanied or followed by fever, headache, rash, nausea, or vomiting, consult a doctor promptly.

Do not use

- with any other drug containing acetaminophen (prescription or nonprescription). If you are not sure whether a drug contains acetaminophen, ask a doctor or pharmacist.
- if you are now taking a prescription monoamine oxidase inhibitor (MAOI) (certain drugs for depression, psychiatric or emotional conditions, or Parkinson's disease), or for 2 weeks after stopping the MAOI drug. If you do not know if your prescription drug contains an MAOI, ask a doctor or pharmacist before taking this product.

Ask a doctor before use if you have

- liver disease
- glaucoma
- cough that occurs with too much phlegm (mucus)
- a breathing problem or chronic cough that lasts or as occurs with smoking, asthma, chronic bronchitis, or emphysema
- trouble urinating due to enlarged prostate gland
- a sodium-restricted diet

Ask a doctor or pharmacist before use if you are

- taking sedatives or tranquilizers
- taking the blood thinning drug warfarin

When using this product

- do not use more than directed
- excitability may occur, especially in children
- marked drowsiness may occur
- avoid alcoholic drinks
- be careful when driving a motor vehicle or operating machinery
- alcohol, sedatives, and tranquilizers may increase drowsiness

Stop use and ask a doctor if

- pain or cough gets worse or lasts more than 7 days
- fever gets worse or lasts more than 3 days
- redness or swelling is present
- new symptoms occur
- cough comes back or occurs with rash or headache that lasts

These could be signs of a serious condition.

If pregnant or breast-feeding,

ask a health professional before use.

Keep out of reach of children.

OVERDOSAGE

In case of overdose, get medical help or contact a Poison Control Center right away. Quick medical attention is critical for adults as well as for children even if you do not notice any signs or symptoms.

Directions

- take only as directed
- only use the dose cup provided
- do not exceed 4 doses per 24 hrs

adults & children 12 yrs & over | 30 mL every 6 hrs
children 4 to under 12 yrs | ask a doctor
children under 4 yrs | do not use

Other information

- each 30 mL contains: sodium 24 mg
- store at no greater than 25°C and do not refrigerate

Inactive ingredients

alcohol, anhydrous citric acid, FD&C Red No. 40, flavor, glycerin, propylene glycol, saccharin sodium, sodium benzoate, sorbitol, sucralose, trisodium citrate dihydrate, water

Questions?

1-800-362-1683

TAMPER EVIDENT: DO NOT USE IF PRINTED SHRINKBAND ON BOTTLE IS BROKEN OR MISSING.

DIST. BY: PROCTER & GAMBLE,

CINCINNATI, OH 45202

Vicks® DayQuil™ INTENSE FLU MULTI-SYMPTOM Liquid

Drug Facts

Active ingredients (in each 30 mL)

Acetaminophen 1000 mg
Dextromethorphan HBr 30 mg

Purpose

Pain reliever/fever reducer
Cough suppressant

Uses

temporarily relieves common cold/flu symptoms:

- cough due to minor throat and bronchial irritation
- sore throat
- headache
- minor aches and pains
- fever

Warnings

Liver warning:

This product contains acetaminophen. Severe liver damage may occur if you take
• more than 3 doses (30 mL each) in 24 hrs, which is the maximum daily amount for this product
• with other drugs containing acetaminophen
• 3 or more alcoholic drinks every day while using this product

Allergy Alert: Acetaminophen may cause severe skin reactions. Symptoms may include:
• skin reddening • blisters • rash

If a skin reaction occurs, stop use and seek medical help right away

Sore throat warning: If sore throat is severe, persists for more than 2 days, is accompanied or followed by fever, headache, rash, nausea, or vomiting, consult a doctor promptly.

Do not use

- with any other drug containing acetaminophen (prescription or nonprescription). If you are not sure whether a drug contains acetaminophen, ask a doctor or pharmacist.
- if you are now taking a prescription monoamine oxidase inhibitor (MAOI) (certain drugs for depression, psychiatric or emotional conditions, or Parkinson's disease), or for 2 weeks after stopping the MAOI drug. If you do not know if your prescription drug contains an MAOI, ask a doctor or pharmacist before taking this product.

Ask a doctor before use if you have

- liver disease
- cough that occurs with too much phlegm (mucus)
- persistent or chronic cough such as occurs with smoking, asthma, or emphysema
- a sodium-restricted diet

Ask a doctor or pharmacist before use if you are

taking the blood thinning drug warfarin

Stop use and ask a doctor if

- pain or cough get worse or lasts more than 7 days
- fever gets worse or lasts more than 3 days
- redness or swelling is present
- new symptoms occur
- cough comes back or occurs with rash or headache that lasts

These could be signs of a serious condition.

If pregnant or breast-feeding,

ask a health professional before use.

Keep out of reach of children.

OVERDOSAGE

In case of overdose, get medical help or contact a Poison Control Center right away. Quick medical attention is critical for adults as well as for children even if you do not notice any signs or symptoms.

Directions

- take only as directed
- only use the dose cup provided
- do not exceed 3 doses (30 mL each) per day (24 hrs)

adults & children 12 yrs & over | 30 mL every 6 hrs
children 4 to under 6 yrs | ask a doctor
children under 4 yrs | do not use

Other information

- each 30 mL contains: sodium 24 mg
- store at no greater than 25ºC (77ºF) and do not refrigerate

Inactive ingredients

alcohol, anhydrous citric acid, FD&C Red No. 40, flavor, glycerin, propylene glycol, saccharin sodium, sodium benzoate, sorbitol, sucralose, trisodium citrate dihydrate, water

Questions?

1-800-362-1683

TAMPER EVIDENT: DO NOT USE IF PRINTED SHRINKBAND ON BOTTLE IS BROKEN OR MISSING.

DIST. BY: PROCTER & GAMBLE,

CINCINNATI, OH 45202

PRINCIPAL DISPLAY PANEL - Convenience Pack

VALUE PACK

VICKS ® DayQuil™ INTENSE FLU

MULTI-SYMPTOM

Acetaminophen, Dextromethorphan HBr

Pain reliever/Fever reducer, Cough suppressant

BODY ACHES

FEVER

HEADACHE

SORE THROAT

COUGH

Daytime Relief

Alcohol 10%

VICKS ® NyQuil ™ INTENSE FLU

MULTI-SYMPTOM

Acetaminophen- Pain reliever/fever reducer

Doxylamine Succinate - Antihistamine

Dextromethorphan HBr - Cough suppressant

BODY ACHES

FEVER

HEADACHE

SORE THROAT

SNEEZING

RUNNY NOSE

COUGH

Nighttime Relief

Alcohol 10%

2 BOTTLES - 12 FL OZ (354 mL) EACH; TOTAL 24 FL OZ (708 mL)